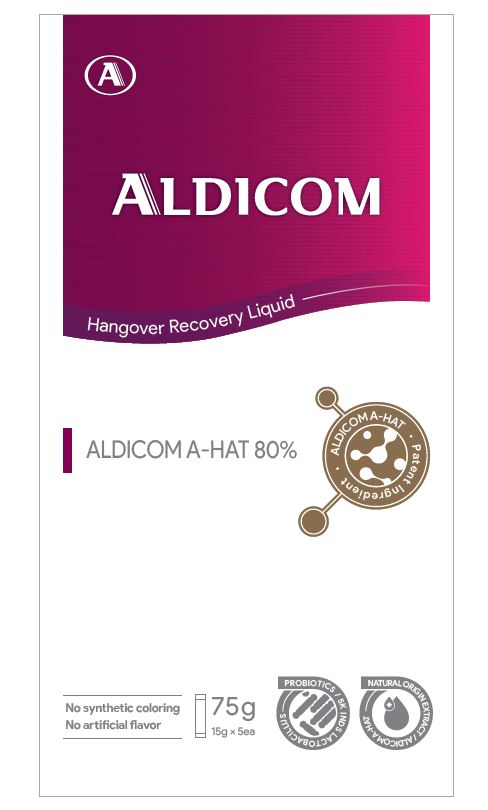 DRUG LABEL: ALDICOM
NDC: 73392-0002 | Form: LIQUID
Manufacturer: NAME
Category: otc | Type: HUMAN OTC DRUG LABEL
Date: 20211227

ACTIVE INGREDIENTS: LACTOBACILLUS PLANTARUM 1 g/100 g
INACTIVE INGREDIENTS: HOVENIA DULCIS WHOLE

Drug Facts

ACTIVE INGREDIENT

ALDICOM A-HAT, lactobacillus

INACTIVE INGREDIENT

fryctiikugisaccgarudem sugar fed honey, glucomannan, pueraria montana var. lobata extract

PURPOSE

Alcohol decomposition

keep out of reach of the children

INDICATIONS AND USAGE

Take 1ea before and after drinking

WARNINGS

Do not take in excess of the specified dose

DOSAGE AND ADMINISTRATION

for oral use only